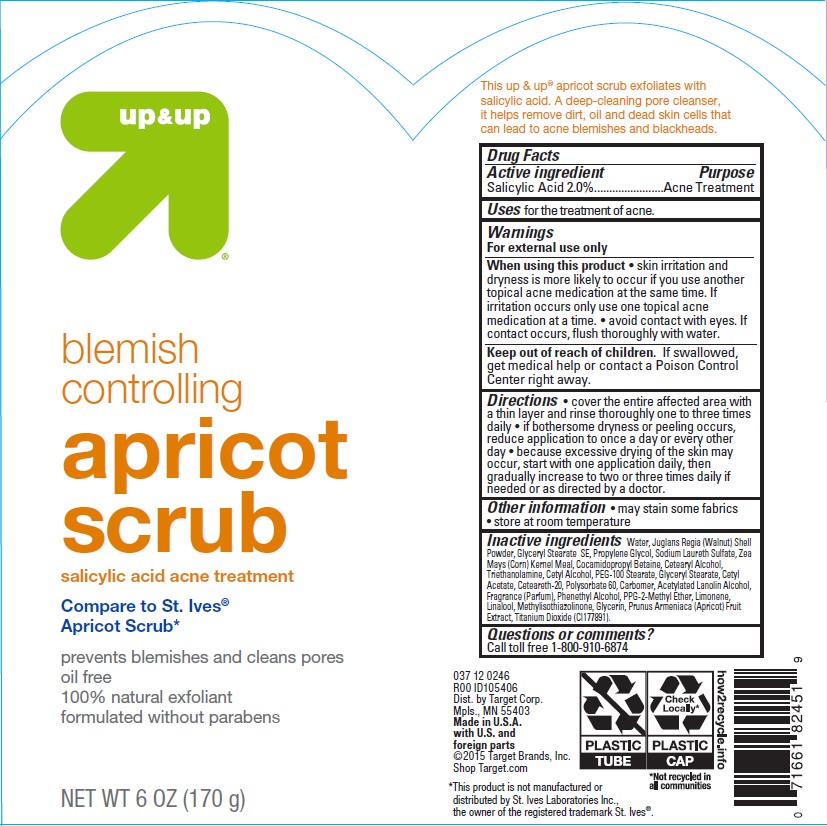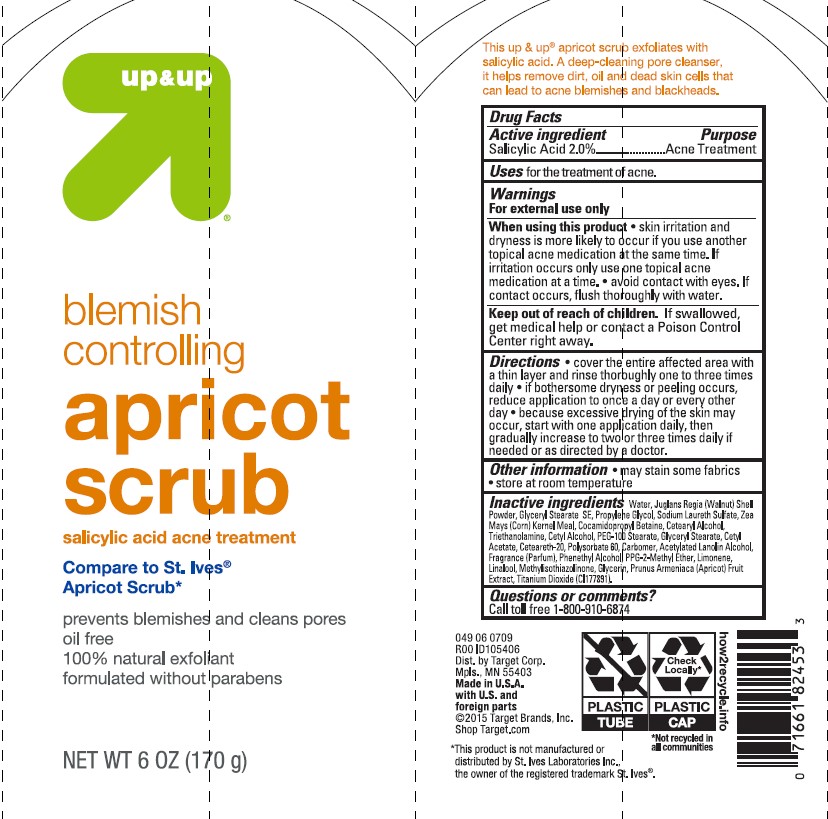 DRUG LABEL: Up and Up
NDC: 11673-930 | Form: EMULSION
Manufacturer: TARGET CORPORATION
Category: otc | Type: HUMAN OTC DRUG LABEL
Date: 20241014

ACTIVE INGREDIENTS: SALICYLIC ACID 20 mg/1 g
INACTIVE INGREDIENTS: POLYOXYL 20 CETOSTEARYL ETHER; TITANIUM DIOXIDE; SODIUM LAURETH SULFATE; CORN GRAIN; GLYCERYL STEARATE SE; COCAMIDOPROPYL BETAINE; PROPYLENE GLYCOL; GLYCERIN; CETYL ALCOHOL; GLYCERYL STEARATE/PEG-100 STEARATE; ACETYLATED LANOLIN ALCOHOLS; METHYLISOTHIAZOLINONE; PPG-2 METHYL ETHER; APRICOT; LIMONENE, (+/-)-; WATER; CARBOMER HOMOPOLYMER TYPE B (ALLYL SUCROSE CROSSLINKED); JUGLANS REGIA SHELL; CETOSTEARYL ALCOHOL; CETYL ACETATE; POLYSORBATE 60; TROLAMINE; PHENYLETHYL ALCOHOL; LINALOOL, (+/-)-

Up & Up Blemish Controlling Apricot Scrub

Active ingredient

Salicylic Acid 2.0%

Purpose

Acne Treatment

Uses

for the treatment of acne.

Warnings

For external use only

When using this product

• skin irritation and dryness is more likely to occur if you use another topical acne medication at the same time. If irritation occurs only use one topical acne medication at a time. • avoid contact with eyes. If contact occurs, flush thoroughly with water.

Keep out of reach of children.

If swallowed, get medical help or contact a Poison Control Center right away.

Directions

• cover the entire affected area with a thin layer and rinse thoroughly one to three times daily• if bothersome dryness or peeling occurs, reduce application to once a day or every other day• because excessive drying of the skin may occur, start with one application daily, then gradually increase to two or three times daily if needed or as directed by a doctor.

Other information

•may stain some fabric •store at room temperature

Inactive ingredients

Water, Juglans Regia (Walnut) Shell Powder, Glyceryl Stearate SE, Propylene Glycol, Sodium Laureth Sulfate, Zea Mays (Corn) Kernel Meal, Cocamidopropyl Betaine, Cetearyl Alcohol, Triethanolamine, Cetyl Alcohol, PEG-100 Stearate, Glyceryl Stearate, Cetyl Acetate, Ceteareth-20, Polysorbate 60, Carbomer, Acetylated Lanolin Alcohol, Fragrance (Parfum), Phenethyl Alcohol, PPG-2-Methyl Ether, Limonene, Linalool, Methylisothiazolinone, Glycerin, Prunus Armeniaca (Apricot) Fruit Extract, Titanium Dioxide (CI177891).

PACKAGE LABEL

Up & Up Blemish Controlling Apricot Scrub

NET WT 6 OZ (170 g)

NDC 11673-930-15